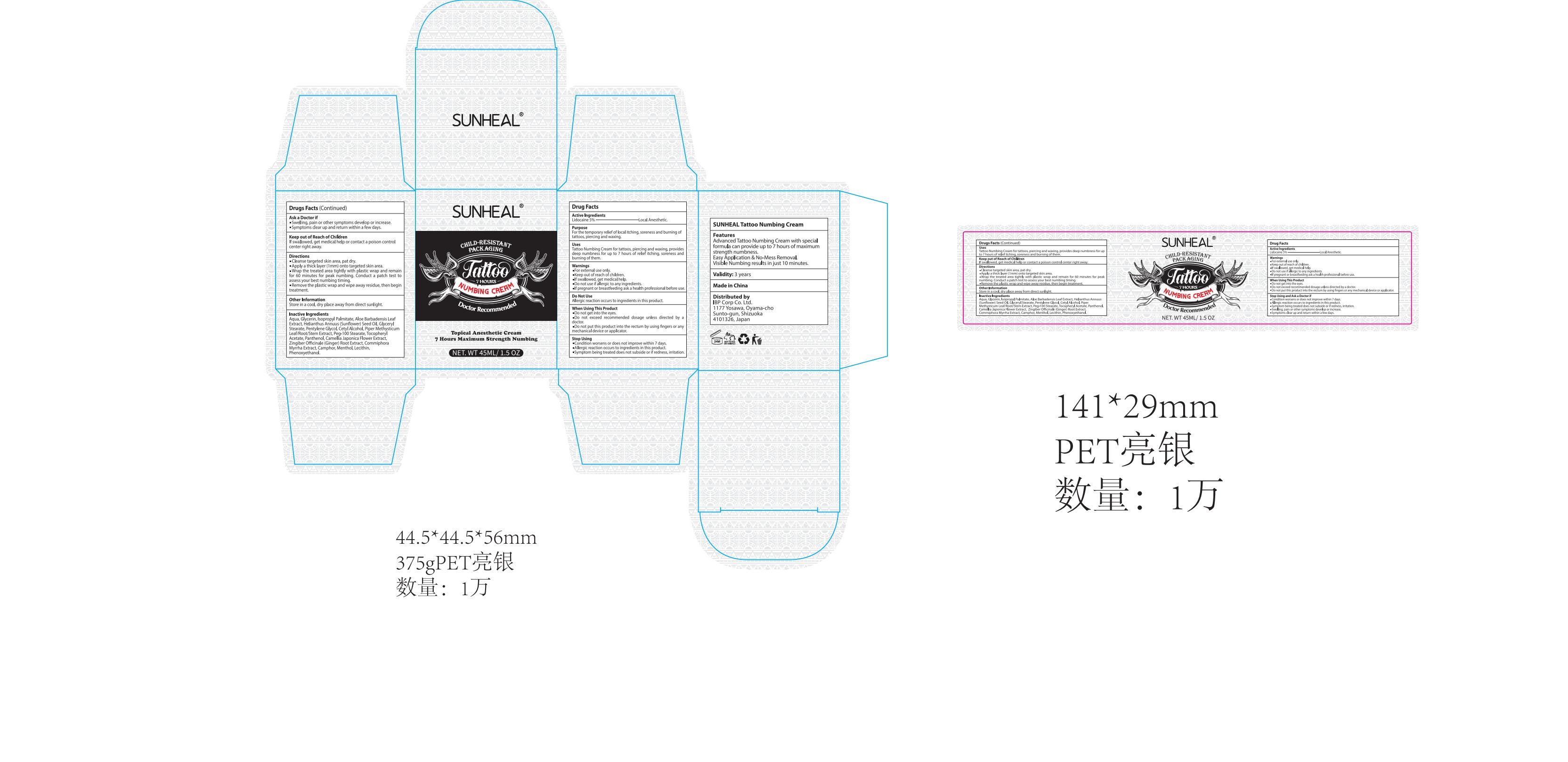 DRUG LABEL: SUNHEAL Tattoo Numbing Cream
NDC: 83871-001 | Form: CREAM
Manufacturer: IBP CORP CO. LTD.
Category: otc | Type: HUMAN OTC DRUG LABEL
Date: 20231219

ACTIVE INGREDIENTS: LIDOCAINE 5 g/100 g
INACTIVE INGREDIENTS: ISOPROPYL PALMITATE; ALPHA-TOCOPHEROL ACETATE; GINGER; CETYL ALCOHOL; MACROPIPER METHYSTICUM ROOT; GLYCERIN; WATER; SUNFLOWER OIL; PENTYLENE GLYCOL; PANTHENOL; MENTHOL; GLYCERYL MONOSTEARATE; ALOE VERA LEAF; POLYOXYL 100 STEARATE; COMMIPHORA MYRRHA WHOLE; CAMPHOR (NATURAL); CAMELLIA JAPONICA FLOWER

83871-001

Active Ingredient

Lidocaine 5%

Purpose

For the temporary relief of local itching, soreness and burning of tattoos, piercing and waxing.

Use

Tattoo Numbing Cream for tattoos, piercing and waxing, provides deep numbness for up to 7 hours of relief itching, soreness and burning of them.

Warnings

For external use only.
Keep out of reach of children.
If swallowed, get medical help.
Do not use if allergic to any ingredients.
If pregnant or breastfeeding ask a health professional before use.

Do not use

Allergic reaction occurs to ingredients in this product.

When Using

Do not get into the eyes.
Do not exceed recommended dosage unless directed by a doctor.
Do not put this product into the rectum by using fingers or any mechanical device or applicator.

Stop Use

Condition worsens or does not improve within 7 days.
Allergic reaction occurs to ingredients in this product.
Symptom being treated does not subside or if redness, irritation.

Ask Doctor

Swelling, pain or other symptoms develop or increase.
Symptoms clear up and return within a few days.

Keep Oot Of Reach Of Children

If swallowed, get medical help or contact a poison control center right away.

Directions

1.Cleanse targeted skin area, pat dry.
2.Apply a thick layer (1mm) onto targeted skin area.
3.Wrap the treated area tightly with plastic wrap and remain for 60 minutes for peak numbing. Conduct a patch test to assess your best numbing timing.
4.Remove the plastic wrap and wipe away residue, then begin treatment.

Other information

Store in a cool, dry place away from direct sunlight.

Inactive ingredients

Aqua, Glycerin, Isopropyl Palmitate, Aloe Barbadensis Leaf Extract,
Helianthus Annuus (Sunflower) Seed Oil, Glyceryl Stearate,
Pentylene Glycol, Cetyl Alcohol, Piper Methysticum Leaf/Root/Stem Extract, Peg-100 Stearate, Tocopheryl Acetate, Panthenol, Camellia Japonica Flower Extract,
Zingiber Officinale (Ginger) Root Extract, Commiphora Myrrha Extract, Camphor, Menthol, Lecithin, Phenoxyethanol.